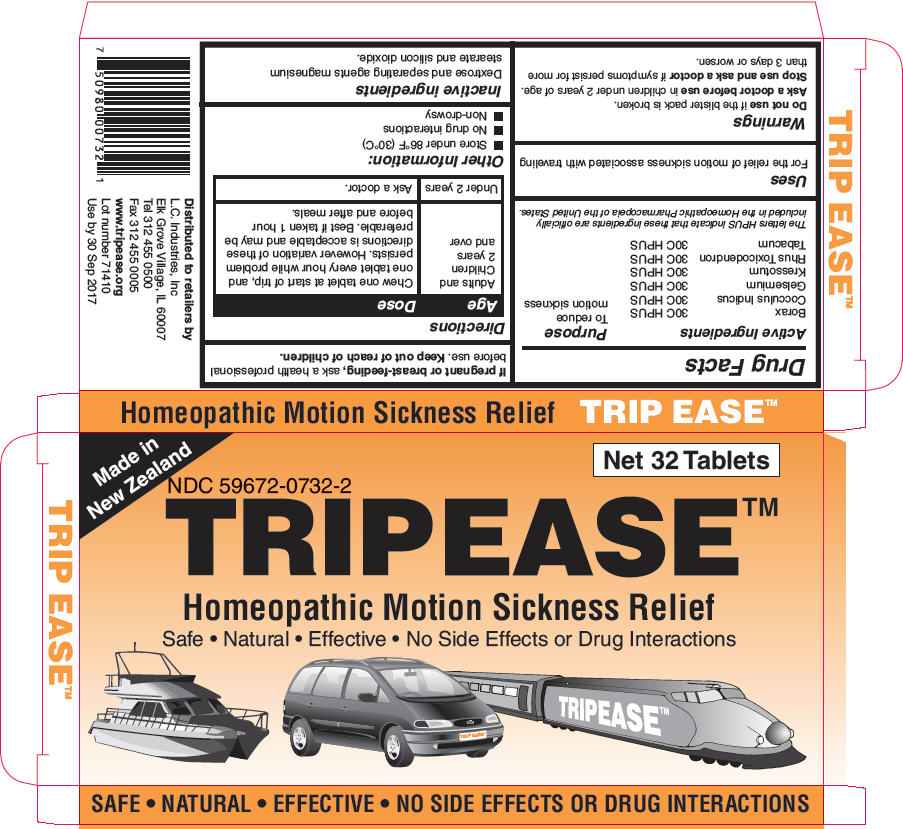 DRUG LABEL: TRIP EASE
NDC: 59672-0732 | Form: TABLET
Manufacturer: LC Industries
Category: homeopathic | Type: HUMAN OTC DRUG LABEL
Date: 20140814

ACTIVE INGREDIENTS: SODIUM BORATE 30 [hp_C]/1 1; ANAMIRTA COCCULUS SEED 30 [hp_C]/1 1; GELSEMIUM SEMPERVIRENS ROOT 30 [hp_C]/1 1; WOOD CREOSOTE 30 [hp_C]/1 1; TOXICODENDRON PUBESCENS LEAF 30 [hp_C]/1 1; TOBACCO LEAF 30 [hp_C]/1 1
INACTIVE INGREDIENTS: Dextrose 242 mg/1 1; Silicon Dioxide; Magnesium stearate

TRIP EASE™

Drug Facts

ACTIVE INGREDIENT

Active Ingredients |  | Purpose
Borax | 30C HPUS | To reduce motion sickness
Cocculus Indicus | 30C HPUS | To reduce motion sickness
Gelsemium | 30C HPUS | To reduce motion sickness
Kressotum | 30C HPUS | To reduce motion sickness
Rhus Toxicodendron | 30C HPUS | To reduce motion sickness
Tabacum | 30C HPUS
The letters HPUS indicate that these ingredients are officially included in the Homeopathic Pharmacopeia of the United States.

Uses

For the relief of motion sickness associated with traveling

Warnings

Do not use if the blister pack is broken.

Ask a doctor before use in children under 2 years of age.

Stop use and ask a doctor if symptoms persist for more than 3 days or worsen.

PREGNANCY OR BREAST FEEDING

If pregnant or breast-feeding, ask a health professional before use.

Keep out of reach of children.

Directions

Age | Dose
Adults and Children 2 years and over | Chew one tablet at start of trip, and one tablet every hour while problem persists. However variation of these directions is acceptable and may be preferable. Best if taken 1 hour before and after meals.
Under 2 years | Ask a doctor.

Other Information

- Store under 86°F (30°C)
- No drug interactions
- Non-drowsy

Inactive ingredients

Dextrose and separating agents magnesium stearate and silicon dioxide.

Distributed to retailers by
L.C. Industries, Inc
Elk Grove Village, IL 60007

PRINCIPAL DISPLAY PANEL - 32 Tablet Blister Pack Carton

Made in
New Zealand

Net 32 Tablets

NDC 59672-0732-2

TRIP EASE™

Homeopathic Motion Sickness Relief
Safe • Natural • Effective • No Side Effects or Drug Interactions